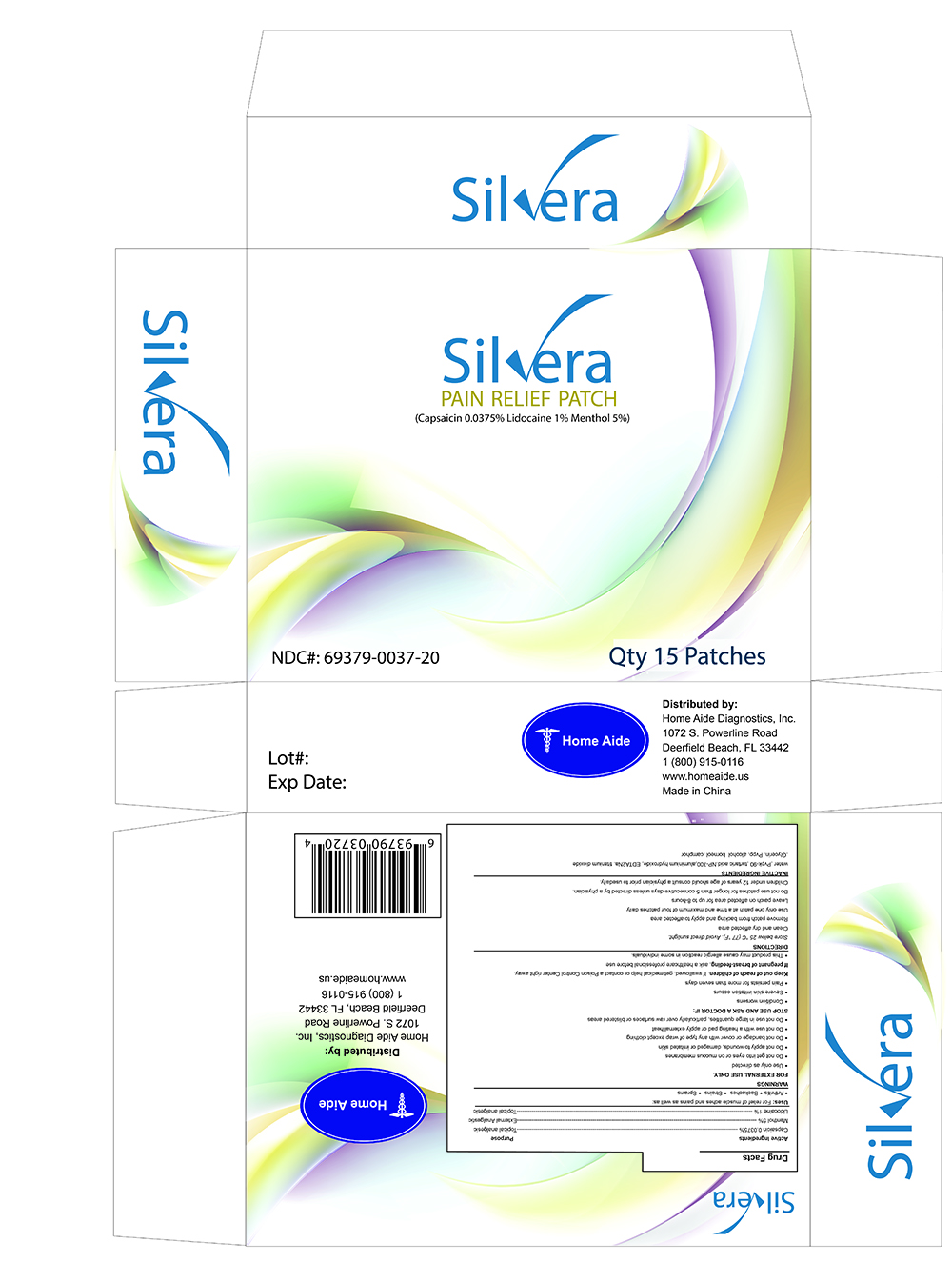 DRUG LABEL: Silvera Pain Relief Patch
NDC: 69379-037 | Form: PATCH
Manufacturer: Home Aide Diagnostics, Inc.
Category: otc | Type: HUMAN OTC DRUG LABEL
Date: 20150528

ACTIVE INGREDIENTS: CAPSAICIN 0.0375 g/100 g; LIDOCAINE 1 g/100 g; MENTHOL 5 g/100 g
INACTIVE INGREDIENTS: BORNEOL

Silvera External Pain Relief Patch

ACTIVE INGREDIENTS

- Capsaicin 0.0375% - Topical Analgesic
- Menthol 5% - External Analgestic
- Lidocaine 1% - Topical Analgesic

USES

- For relief of muscle aches and pains as well as:
- Arthritis
- Backaches
- Strains
- Sprains

WARNINGS

- Do not get into eyes or on mucous membranes
- Do not apply to wounds, damaged or irritated skin
- Do not bandage or cover with any type of wrap except clothing
- Do not use with a heating pad or apply external heat
- Do not use in large quantities, particularly over raw surfaces or blistered areas
- This product may cause allergic reaction in some individuals

STOP USE AND ASK A DOCTOR IF

- Condition worsens
- Severe skin irritation occurs
- Pain persists for more than seven days

KEEP OUT OF REACH OF CHILDREN

- If swallowed, get medical help or contact a poison control center right away

IF PREGNANT OR BREAST-FEEDING

- Ask a healthcare professional before use

DIRECTIONS

- Store below 25oC (77 oF). Avoid direct sunlight
- Clean and dry affected area
- Remove patch from backing and apply to affected area
- Use only one patch at a time and maximum of four patches daily
- Leave patch on affeted area for up to 8-hours
- Do not use patch for longer than 5 consecutive days unless directed by a physician
- Children under 12 years of age should consult a physician prior to use

INACTIVE INGREDIENTS

- Water
- Pvpk-90
- tartaric acid
- NP-700
- Aluminium hydroxide
- EDTA2Na
- Titanium dioxide
- Glycerin
- Pvpp
- Alcohol borneol
- Camphor

PURPOSE

- FOR EXTERNAL USE ONLY
- Use only as directed